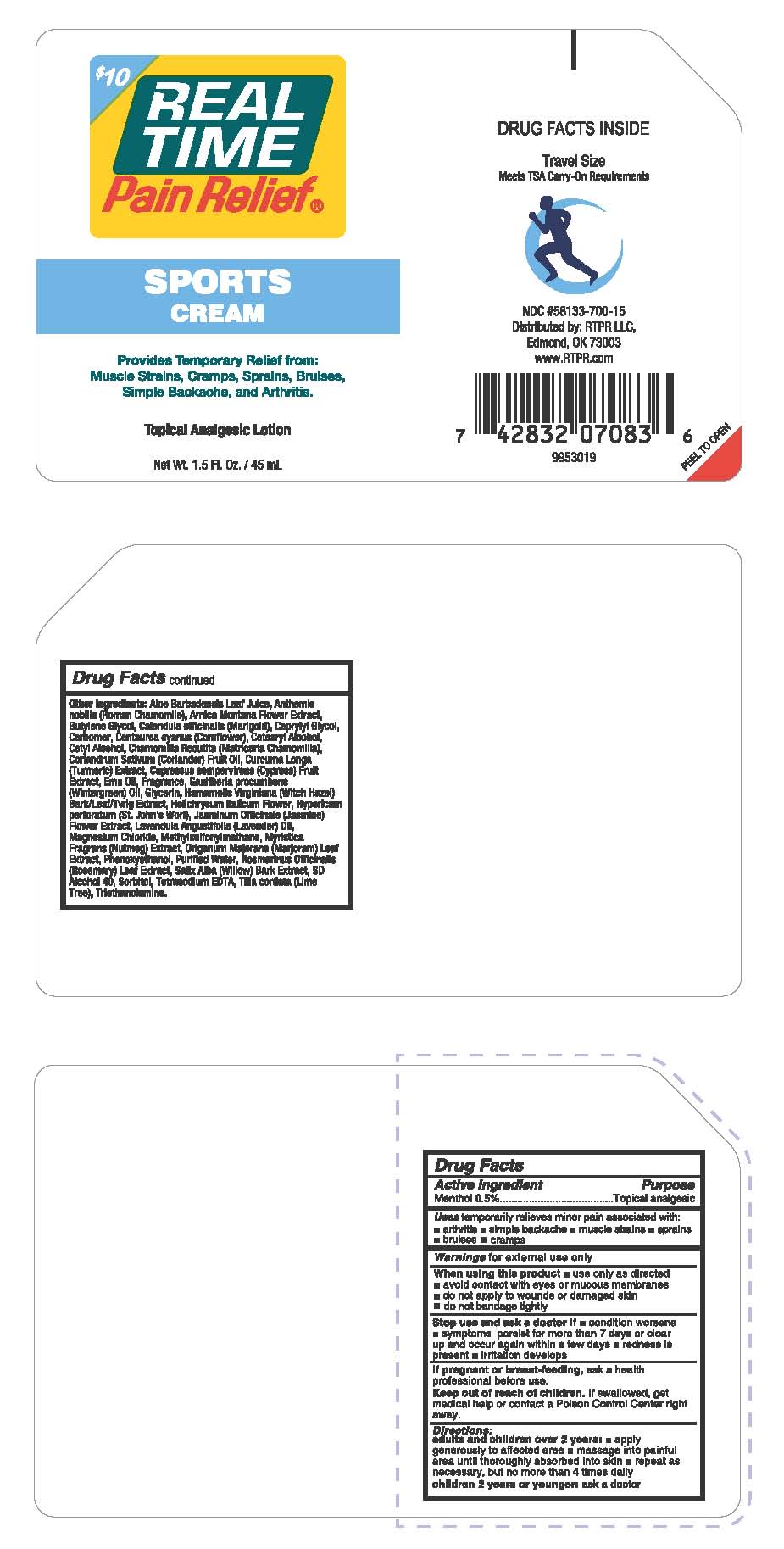 DRUG LABEL: Real Time Pain Relief Sports Cream
NDC: 58133-700 | Form: LOTION
Manufacturer: Cosmetic Specialty labs, Inc.
Category: otc | Type: HUMAN OTC DRUG LABEL
Date: 20180102

ACTIVE INGREDIENTS: MENTHOL 0.5 g/100 mL
INACTIVE INGREDIENTS: ALOE VERA LEAF; CHAMAEMELUM NOBILE FLOWER; ARNICA MONTANA FLOWER; CALENDULA OFFICINALIS FLOWER; CARBOMER 934; CENTAUREA CYANUS FLOWER; CETOSTEARYL ALCOHOL; CETYL ALCOHOL; CORIANDER OIL; MAGNESIUM CHLORIDE; EMU OIL; GLUCOSAMINE HYDROCHLORIDE; HAMAMELIS VIRGINIANA TOP; WATER; SALIX ALBA BARK; SORBITOL; TILIA X EUROPAEA FLOWER; MYRISTICA FRAGRANS WHOLE; TETRASODIUM DIETHYLENETRIAMINEPENTAMETHYLENEPHOSPHONATE; BUTYLENE GLYCOL; CAPRYLYL GLYCOL; CURCUMA LONGA LEAF; DIMETHYL SULFONE; 2-(DIPROPYLAMINO)ETHANOL; HELICHRYSUM ITALICUM FLOWER; JASMINUM OFFICINALE FLOWER; LAVENDER OIL; ORIGANUM MAJORANA; PHENOXYETHANOL; ROSMARINUS OFFICINALIS FLOWERING TOP OIL; TRIETHANOLAMINE TRIS(DIHYDROGEN PHOSPHATE); HYPERICUM PERFORATUM; ANTHEMIS ARVENSIS FLOWERING TOP; CUPRESSUS SEMPERVIRENS LEAF OIL; GAULTHERIA PROCUMBENS LEAF; GLYCERIN

Real Time Pain Relief Sports Cream

ACTIVE INGREDIENT

Menthol 0.5%

PURPOSE

Topical analgesic

KEEP OUT OF REACH OF CHILDREN

If swallowed, get medical help or contact a poison control center right away.

USES

Temporarily relieves minor pain associated with

- arthritis
- simple backache
- muscle strains
- sprains
- bruises

WARNINGS

for external use only

When using this product

- use only as directed
- avoid contact with eyes or mucus membranes
- do not apply to wounds or damaged skin
- do not bandage tightly

Stop using and ask a doctor if

- condition worsens
- symptoms persist for more than 7 days or clear up and occur again within a few days
- redness is present
- irritation develops

If pregnant or breast-feeding

ask a health professional before use

DIRECTIONS

adults and children over 2 years

- apply generously to affected area
- massage into painful area until throughly absorbed into skin
- repeat as necessary, but no more than 4 times daily

children 2 years or younger: ask a doctor

children 12 years or younger

ask a doctor

INACTIVE INGREDIENTS

Aloe Barbadensis Leaf Juice, Anthemis nobilis (Roman Chamomile), Arnica Montana Flower Extract, Butylene Glycol, Calendula officianlis (Marigold), Caprylyl Glycol, Carbomer, Centaurea cyanus (Cornflower), Cetearyl Alcohol, Cetyl Alcohol, Chamomilla Recutita (Matricaria Chamomilla), Coriandrum Sativum (Coriander) Fruit Oil, Curcuma Longa (Turmeric) Extract, Cupressus sempervirens (Cypress) Fruit Extract, Emu Oil, Fragrance, Gaultheria procumbens (Wintergreen) Oil, Glycerin, Hamamelis Virginiana (Witch Hazel) Bark/Leaf/Twig Extract, Helichrysum Italicum Flower, Hypericum perforatum (St. John’s Wort), Jasminum Officianale (Jasmine) Flower Extract, Lavendula Angustifolia (Lavender) Oil, Magnesium Chloride, Methylsulfonylmethane, Myristica Fragrans (Nutmeg) Extract, Origanum Majorana (Marjoram) Leaf Extract, Phenoxyethanol, Purified Water, Rosmarinus Officinalis (Rosemary) Leaf Extract, Salix Alba (Willow) Bark Extract, SD Alcohol 40, Sorbitol, Tetrasodium EDTA, Tilia cordata (Lime Tree), Triethanolamine.